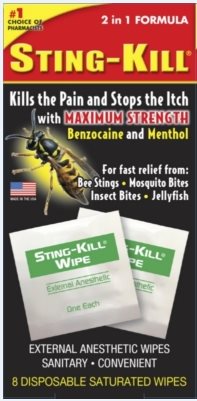 DRUG LABEL: Sting-Kill
NDC: 52412-250 | Form: SOLUTION
Manufacturer: Randob Ltd.
Category: otc | Type: HUMAN OTC DRUG LABEL
Date: 20170213

ACTIVE INGREDIENTS: BENZOCAINE 200 mg/1 mL; MENTHOL 10 mg/1 mL
INACTIVE INGREDIENTS: FD&C BLUE NO. 1; ISOPROPYL ALCOHOL; PEG-8 LAURATE; WATER

Drug Facts

Active ingredients

Benzocaine USP 20%

Menthol USP 1%

Purpose

(for pain) Topical Anesthetic

(anti-itch) Antipruritic

Keep Out of Reach of Children

If swallowed get medical help or contact Poison Control Center right away.

Uses

- Temporarily relieves pain and itching of bee stings, insect bites and minor skin irritations.

Warnings

- For external use only
- Avoid contact with eyes

Get medical help right away if

- You are sensitive to insect venom. You may develop a serious reaction when stung.

Stop use and ask a doctor if

- Condition worsens
- Symptoms last for more than 7 days

Directions

Children under 2 yrs.

- Do not use
- Consult doctor

Adults and children 2 yrs. and older

- Apply to affected area as needed but not more than 3 to 4 times a day.
- (1) Bee stings only, remove stinger before treatment.
- (2) Tear foil pack at notch, exposing pad.
- (3) Apply immediately to bite or sting area. Dispose of pad after use.

Inactive Ingredients

FD&C Blue #1, FD&C Yellow #5, Isopropyl Alcohol 15%, PEG-8, Water.

Package/Label Principal Display Panel

#1 CHOICE OF PHARMACISTS

2 in 1 FORMULA

STING-KILL®

Kills the Pain and Stops the Itch with MAXIMUM STRENGTH Benzocaine and Menthol

For fast relief from:

Bee Stings • Mosquito Bites

Insect Bites • Jellyfish

MADE IN THE USA

EXTERNAL ANESTHETIC WIPES

SANITARY• CONVENIENT

8 DISPOSABLE SATURATED WIPES